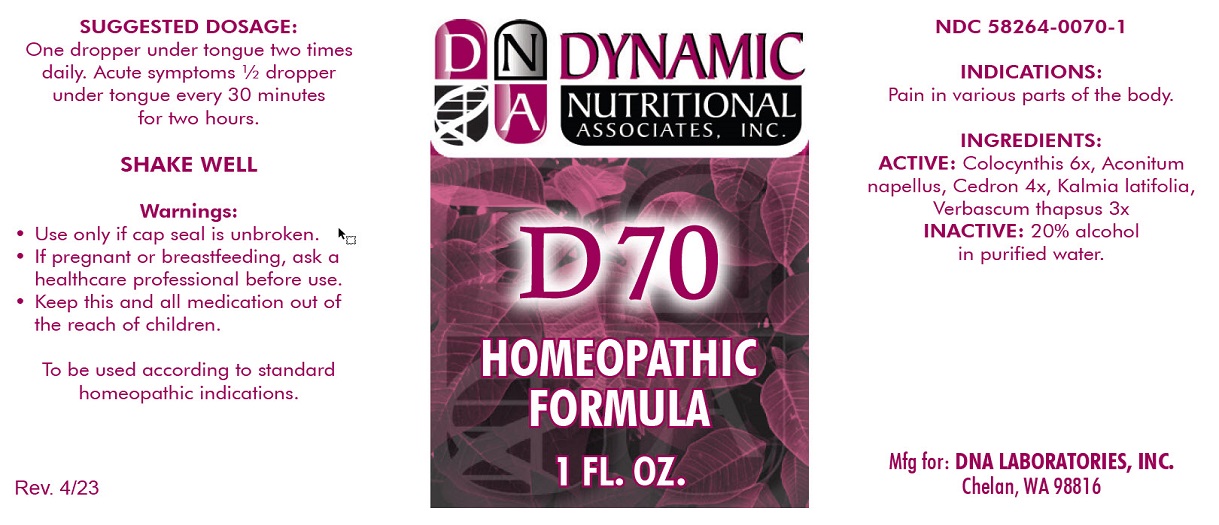 DRUG LABEL: D-70
NDC: 58264-0070 | Form: SOLUTION
Manufacturer: DNA Labs, Inc.
Category: homeopathic | Type: HUMAN OTC DRUG LABEL
Date: 20250113

ACTIVE INGREDIENTS: ACONITUM NAPELLUS 4 [hp_X]/1 mL; SIMABA CEDRON SEED 4 [hp_X]/1 mL; CITRULLUS COLOCYNTHIS FRUIT PULP 6 [hp_X]/1 mL; KALMIA LATIFOLIA LEAF 3 [hp_X]/1 mL; VERBASCUM THAPSUS 3 [hp_X]/1 mL
INACTIVE INGREDIENTS: ALCOHOL; WATER

D-70

NDC 58264-0070-1

INDICATIONS

PURPOSE

Pain in various parts of the body.

INGREDIENTS

ACTIVE

Colocynthis 6x, Aconitum napellus, Cedron 4x, Kalmia latifolia, Verbascum thapsus 3x

INACTIVE

20% alcohol in purified water.

SUGGESTED DOSAGE

One dropper under tongue two times daily. Acute symptoms ½ dropper under tongue every 30 minutes for two hours.

STORAGE AND HANDLING

SHAKE WELL

Warnings

- Use only if cap seal is unbroken.

PREGNANCY OR BREAST FEEDING

- If pregnant or breastfeeding, ask a healthcare professional before use.

KEEP OUT OF REACH OF CHILDREN

- Keep this and all medication out of the reach of children.

To be used according to standard homeopathic indications.

PRINCIPAL DISPLAY PANEL - 1 FL. OZ. Bottle Label

DYNAMIC
NUTRITIONAL
ASSOCIATES, INC.

D-70

HOMEOPATHIC
STRESS FORMULA

1 FL. OZ.